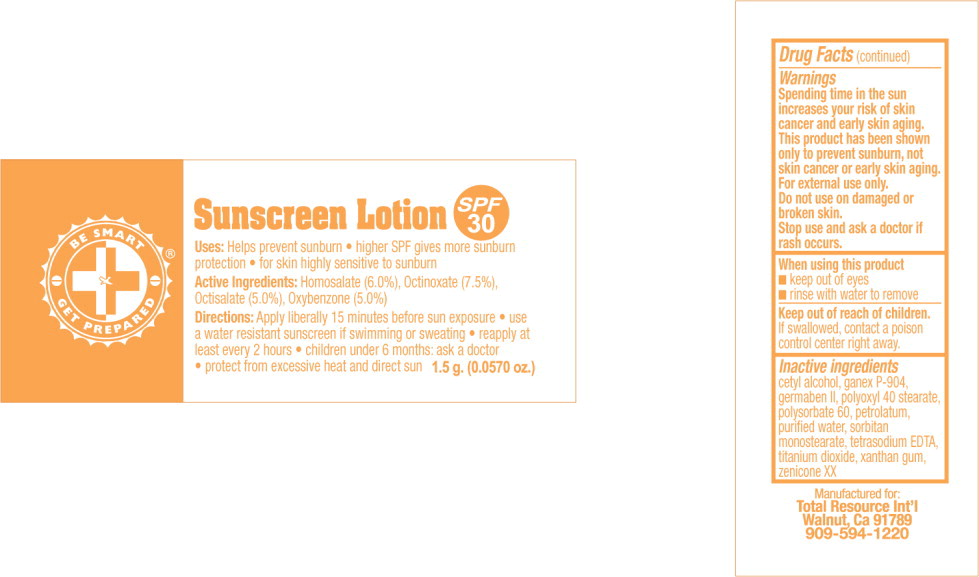 DRUG LABEL: Sunscreen
NDC: 55550-102 | Form: LOTION
Manufacturer: Total Resources International
Category: otc | Type: HUMAN OTC DRUG LABEL
Date: 20241220

ACTIVE INGREDIENTS: HOMOSALATE 6 mg/1 g; OCTINOXATE 7.5 mg/1 g; OCTISALATE 5 mg/1 g; OXYBENZONE 5 mg/1 g
INACTIVE INGREDIENTS: CETYL ALCOHOL; POVIDONE K30; PROPYLENE GLYCOL; PROPYLPARABEN; METHYLPARABEN; DIAZOLIDINYL UREA; POLYOXYL 40 STEARATE; POLYSORBATE 60; PETROLATUM; WATER; SORBITAN MONOSTEARATE; EDETATE SODIUM; TITANIUM DIOXIDE; XANTHAN GUM; POLYETHYLENE GLYCOL 400; DIMETHICONE

Sunscreen

Drug Facts

Uses

PURPOSE

- helps prevent sunburn
- higher SPF gives more sunburn protection
- for skin highly sensitive to sunburn

Active Ingredients

Homosalate (6.0%), Octinoxate (7.5%), Octisalate (5.0%), Oxybenzone (5.0%)

Directions

- apply liberally 15 minutes before sun exposure
- use a water resistant sunscreen if swimming or sweating
- reapply at least every 2 hours
- children under 6 months: ask a doctor
- protect from excessive heat and direct sun

Warnings

Spending time in the sun increases your risk of skin cancer and early skin aging. This product has been shown only to prevent sunburn, not skin cancer or early skin aging.
For external use only.

Do not use on damaged or broken skin.

Stop use and ask a doctor if rash occurs.

When using this product

- keep out of eyes
- rinse with water to remove

Keep out of reach of children.

if swallowed, conatct a poison control center right away

Do not use on damaged or broken skin.

Stop use and ask a doctor if rash occurs.

When using this product

- keep out of eyes
- rinse with water to remove

Keep out of reach of children.

If swallowed, contact a poison control center right away

Inactive ingredients

cetyl alcohol, ganex P-904, germaben II, polyoxyl 40 stearate, polysorbate 60, petrolatum, purified water, sorbitan monostearate, tetrasodium EDTA, titanium dioxide, xanthan gum, zenicone XX

PRINCIPAL DISPLAY PANEL – packet

Sunscreen Lotion
SPF 30

1.5 g. (0.0570 oz.)